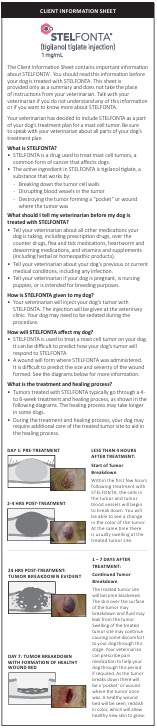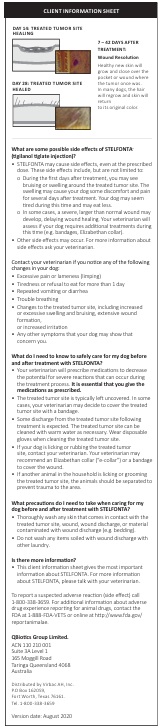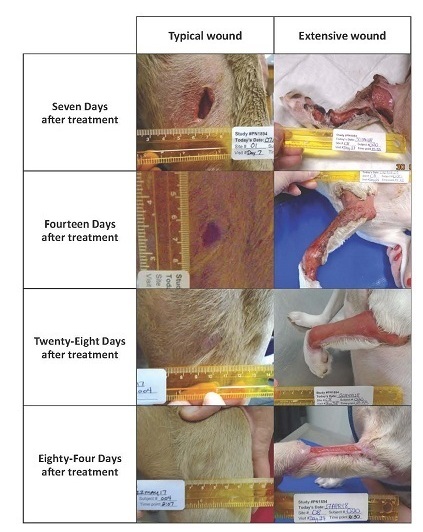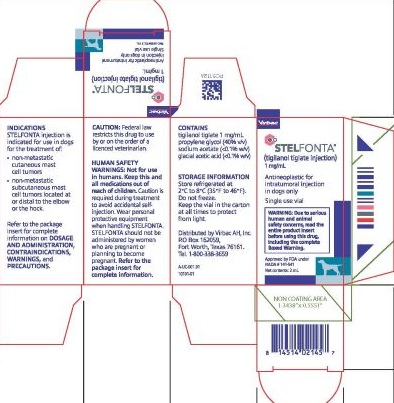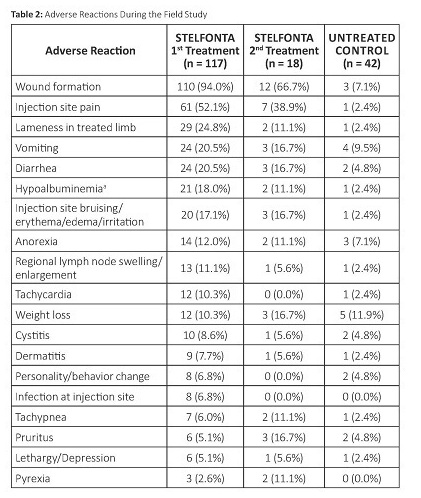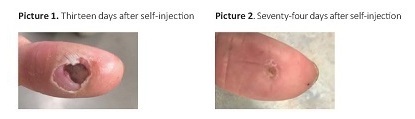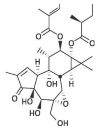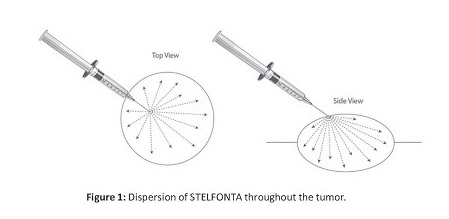 DRUG LABEL: STELFONTA 1 mg/mL
NDC: 51311-993 | Form: SOLUTION
Manufacturer: Virbac AH Inc
Category: animal | Type: PRESCRIPTION ANIMAL DRUG LABEL
Date: 20251003

ACTIVE INGREDIENTS: TIGILANOL TIGLATE 1 mg/1 mg

STELFONTA® (tigilanol tiglate injection)

STELFONTA® (tigilanol tiglate injection)

For intratumoral injection in dogs only
Antineoplastic
Single use vial

WARNING: SEVERE WOUND FORMATION IN HUMANS; EXTENSIVE WOUND FORMATION, MAST CELL DEGRANULATION, AND DEATH IN DOGS DUE TO MAST CELL DEGRANULATION

Human Safety

- Accidental self-injection of STELFONTA® may cause severe wound formation. To decrease the risk of accidental self-injection, sedation of the dog may be necessary (see Dosage and Administration, Human Warnings and Adverse Reactions).

Dog Safety

- Always administer a corticosteroid (e.g. prednisone or prednisolone), an H1 receptor blocking agent (e.g. diphenhydramine), and an H2 receptor blocking agent (e.g. famotidine) when treating with STELFONTA to decrease the potential for severe systemic adverse reactions, including death, from mast cell degranulation (see Contraindications and Dosage and Administration).
- Do not inject STELFONTA into subcutaneous mast cell tumors located above the elbow or hock (e.g. on the body, head, or neck). This may result in accumulation of necrotic debris in the subcutaneous space increasing the risk of systemic adverse reactions, including death, from mast cell degranulation (see Contraindications, Warnings and Adverse Events).
- Treatment with STELFONTA has been associated with cellulitis and severe tissue sloughing extending away from the treated site resulting in extensive wounds that require additional treatment and prolonged recovery times (see Warnings, Precautions and Adverse Events).

CAUTION

Federal law restricts this drug to use by or on the order of a licensed veterinarian.

DESCRIPTION

The active ingredient for tigilanol tiglate injection is a phorbol ester that activates alpha, beta I, beta II, and gamma isoforms of protein kinase C. The chemical name is (4S,5S,6R,7S,8R,9R,10S,11R,12R,13S,14R)-12-(2E)-2-methylbut-2-enoatyl-13- [(2S)-2-methylbutyroyl]-6,7-epoxy-4,5,9,12,13,20-hexahydroxy-1-tigliaen-3-one. The molecular formula is C30H42O10 and its molecular weight is 562.65 g mol-1. Each mL of STELFONTA contains 1 mg tigilanol tiglate and sterile water for injection (60% v/v), propylene glycol (40% v/v), sodium acetate (<0.1% w/v), and glacial acetic acid (<0.1% w/v).

The chemical structure for tigilanol tiglate is:

<p class="First">The active ingredient for tigilanol tiglate injection is a phorbol ester that activates alpha, beta I, beta II, and gamma isoforms of protein kinase C. The chemical name is (4S,5S,6R,7S,8R,9R,10S,11R,12R,13S,14R)-12-(2E)-2-methylbut-2-enoatyl-13- [(2S)-2-methylbutyroyl]-6,7-epoxy-4,5,9,12,13,20-hexahydroxy-1-tigliaen-3-one. The molecular formula is C30H42O10 and its molecular weight is 562.65 g mol-1. Each mL of STELFONTA contains 1 mg tigilanol tiglate and sterile water for injection (60% v/v), propylene glycol (40% v/v), sodium acetate (&lt;0.1% w/v), and glacial acetic acid (&lt;0.1% w/v).</p><p>The chemical structure for tigilanol tiglate is:</p>

INDICATION

STELFONTA injection is indicated for use in dogs for the treatment of:

- non-metastatic cutaneous mast cell tumors
- non-metastatic subcutaneous mast cell tumors located at or distal to the elbow or the hock

DOSAGE AND ADMINISTRATION

ALWAYS PROVIDE THE CLIENT INFORMATION SHEET TO THE DOG OWNER
BEFORE DOSE ADMINISTRATION.

Concomitant medications

Administer the following medications to decrease the potential for severe systemic adverse reactions from mast cell degranulation:

- Corticosteroid (e.g. oral prednisone or prednisolone at anti-inflammatory dose): Start medication 2 days prior to STELFONTA treatment and continue for 8 days post-treatment (10 days total).
- H1 receptor blocking agent (e.g. oral diphenhydramine): Start medication on the day of STELFONTA treatment and continue for a total of 8 days.
- H2 receptor blocking agent (e.g. oral famotidine): Start medication on the day of STELFONTA treatment and continue for a total of 8 days.

Dosing Instructions

Administer STELFONTA as an intratumoral injection at a dose of 0.5 mL per cm3 of tumor volume, as determined by the following calculations:

- Determine the Tumor Volume in cm3:

0.5 x [length (cm) x width (cm) x height (cm)]

- Confirm the Tumor Volume does not exceed 10 cm3. Do not use STELFONTA if tumor volume is >10 cm3.
- Calculate the Dose Volume (mL) of STELFONTA to inject:

Tumor Volume x 0.5 mL

- Confirm the dose of STELFONTA does not exceed 0.25 mL/kg body weight.
- Do not exceed 5 mL per dog, regardless of tumor volume or body weight.
- The minimum dose of STELFONTA is 0.1 mL, regardless of tumor volume or body weight. If the calculated dose is <0.1 mL, administer 0.1 mL

Administration of STELFONTA:

Sedation may be necessary to safely and accurately administer STELFONTA to decrease the chance of accidental self-injection. Wear gloves, eye protection, and lab coat or gown in the preparation and administration of STELFONTA. Care should be taken to restrict injections to the tumor only. STELFONTA should not be injected into the margins, beyond the periphery, or deep to the tumor.

- Shave the tumor site. Avoid manipulation of the tumor.
- Draw the calculated volume of STELFONTA into a sterile Luer-lock syringe with a 23 gauge needle.
- Identify an appropriate injection point on the edge of the tumor. See Figure 1. Insertion of the needle depends on the tumor’s location, form, and appearance. If a tumor protrudes above the surface of the skin, insert the needle at an oblique angle of approximately 45°.
- Insert and embed the needle in the tumor through a single injection site and draw the syringe plunger back slightly to ensure STELFONTA is not injected into a blood vessel. While applying even pressure on the syringe plunger move the needle back and forth in a fanning manner to inject STELFONTA into the tumor. See Figure 1. The drug should fully perfuse the entire tumor.
- When the total dose of STELFONTA has been administered, pause to allow tissue dispersion before removing the needle from the tumor. Pull back on the syringe plunger to create a small negative pressure before removing the needle to minimize leakage from the injection site.
- After the needle is withdrawn, apply light pressure for 30 seconds over the needle exit hole using a gloved finger. If leakage does occur, rinse injection site with saline to wash STELFONTA from the skin surface. Do not readminister.
- To minimize risk of accidental self-injection, do not recap the needle. Disposeof the needle and syringe.

CONTRAINDICATIONS

Do not inject STELFONTA into subcutaneous mast cell tumors located above the elbow or hock (e.g. on the body, head, or neck). This may result in accumulation of necrotic debris in the subcutaneous space increasing the risk of systemic adverse reactions, including death, from mast cell degranulation (see Adverse Reactions).

WARNINGS

Human Safety

NOT FOR USE IN HUMANS. KEEP THIS AND ALL MEDICATIONS OUT OF REACH OF CHILDREN.

Caution is required during treatment to avoid accidental self-injection. Dogs undergoing treatment with STELFONTA should be adequately restrained and sedation used if necessary. Use a Luer-lock syringe to administer STELFONTA. Do not recap the needle. Accidental self-injection may result in local inflammatory reactions, including swelling, redness and severe wound formation. In case of accidental self-injection, immediately rinse the area with water, seek medical advice immediately, and show the package insert to the physician.

Wear personal protective equipment consisting of disposable gloves, protective eye wear, and a lab coat or gown when handling STELFONTA. STELFONTA is an irritant and accidental exposure to skin, eye, or by ingestion should be avoided. In case of dermal or ocular exposure, repeatedly wash the exposed skin or eye with water. If wearing contacts, rinse the eyes first then remove contacts and continue to rinse with water. If symptoms such as local signs of redness and swelling occur, or if there has been ingestion, seek the advice of a physician and show them the package insert.

Limited data is available on the potential teratogenic effects of STELFONTA. Therefore, STELFONTA should not be administered by women who are pregnant or planning to become pregnant.

People with known hypersensitivity to tigilanol tiglate or to any of the excipients should avoid contact with STELFONTA.

Animal Safety

Dogs should be monitored during and for 5-7 days after intratumoral treatment with STELFONTA for signs of systemic mast cell degranulation such as vomiting, diarrhea, lethargy, anorexia/hyporexia, altered breathing, hypotension, urticaria, edema at or away from the treated site, or bruising at or away from the treated site. If signs are observed, appropriate treatment should be started immediately.

Always administer the recommended concomitant medications (corticosteroids, H1, and H2 receptor blocking agents) with STELFONTA. Death has occurred following mast cell degranulation when these concomitant medications were not administered according to this Package Insert (see Dosage and Administrationand Adverse Reactions).

STELFONTA can induce a substantial local inflammatory reaction which may result in pain, bruising, and swelling. During this time, an analgesic may be needed in addition to the use of corticosteroids and both H1 and H2 receptor blocking agents.

Treatment with STELFONTA causes tumor necrosis which is part of the mechanism of action of the drug. Bruising, heat, pain, and swelling may begin at the site within 2 hours of treatment. By day 7 after treatment, wound formation including full thickness dermal necrosis with exudate, peripheral tissue edema, erythema, skin discoloration, tissue sloughing, and necrotic eschar may occur. In addition to tumor necrosis, treatment with STELFONTA has been associated with cellulitis and severe tissue sloughing extending away from the treated site resulting in extensive wounds (see Adverse Reactions).

Do not inject STELFONTA into normal subcutaneous tissue or adjacent tissues (e.g. beyond tumor margins) because severe edema, erythema and necrosis of the injected tissue may occur.

PRECAUTIONS

STELFONTA has not been evaluated in dogs with signs of systemic disease due to the mast cell tumor(s).

STELFONTA is not intended for the treatment of metastatic mast cell tumors.

The safe and effective use of STELFONTA has not been evaluated for simultaneous treatment of more than one mast cell tumor.

The safe and effective use of STELFONTA has not been evaluated in dogs with a mast cell tumor volume >10 cm3.

Use STELFONTA with caution in tumors located within mucocutaneous regions (e.g., eyelids, vulva, prepuce, and anus) as tumor necrosis couldcause a change in morphology of the mucocutaneous region resulting in loss of functional integrity.

Use STELFONTA with caution in mast cell tumors with significant ulceration as leakage of the drug from the ulcerated area may occur following treatment potentially reducing effectiveness.

The safe use of STELFONTA has not been evaluated in dogs with concurrent diseases that may result in delayed wound healing.

After treatment with STELFONTA, dogs may require additional care of the treated site to aid in the healing process. An Elizabethan collar or a non-constricting dry gauze bandage may be needed to prevent the dog from self-traumatizing the treated site.

After treatment with STELFONTA, separation from other household animals may be necessary to prevent grooming and trauma to the treated site.

The safe use of STELFONTA under conditions of use has not been evaluated in dogs younger than 3.5 years old.

The safe use of STELFONTA has not been evaluated in dogs that are pregnant, lactating, or intended for breeding.

ADVERSE REACTIONS

Human Exposure

There was one human exposure during the field study where the veterinarian had a needle stick injury to the thumb at completion of tumor treatment and was injected with an unknown amount of STELFONTA. The incident resulted in pain and necrosis of the center of the thumb at the point of needle stick. The wound healed over a period of three months. See Pictures 1 and 2 below. A separate needle stick injury was reported with a maximum potential dose of 0.1 mL tigilanol tiglate into the distal extremity of the left index finger, resulting in a localized burning sensation, local inflammation, bruising, muscular pain up the left arm, and localized tissue necrosis. Muscular pain resolved in the first 12-24 hours and the wound healed in 8 weeks. There have been other needle stick injuries reported, with at least one injection into a thumb, with minimal (stinging, pain, and swelling) to no adverse events associated with these accidental self-injections.

Field Study

In a well-controlled, multi-center, randomized, double-masked field study evaluating the effectiveness and safety of STELFONTA for the treatment of cutaneous and subcutaneous mast cell tumors in dogs, 117 dogs treated with STELFONTA and 42 dogs receiving sham treatment (untreated control) were evaluated for safety. Eighty-one dogs were treated with STELFONTA on Day 0. Thirty-six previously untreated control dogs were treated with STELFONTA on Day 30. In addition, 18 dogs treated with STELFONTA on Day 0 had the same tumor re-treated with STELFONTA on Day 30 due to incomplete response. The most common adverse reactions included wound formation, injection site pain, lameness in the treated limb, vomiting, diarrhea, and hypoalbuminemia. Wound formation, vomiting, and diarrhea were mainly observed within the first 7 to 10 days after treatment. Injection site pain and lameness in the treated leg were mainly observed within the first 2 days after treatment. Hypoalbuminemia was mainly observed within the first 28 days after treatment. All dogs received concomitant medications as noted in the Effectiveness section. The adverse reactions during the study are summarized in Table 2 below.

a There was a statistically significant decrease in albumin and albumin/globulin ratios at Day 7 in the STELFONTA group compared to the control group. The hypoalbuminemia ranged from 2.0 to 2.6 g/dL (reference range 2.7-3.9 g/dL). Note: If an animal experienced the same adverse reaction more than once, onlythe highest grade was tabulated.

Adverse reactions were graded using the Veterinary Co-operative Oncology Group – Common Terminology Criteria for Adverse Events (VCOG-CTCAE).1 Most adverse reactions were Grade 1 (mild) or 2 (moderate). Grade 3 (severe) and 4 (life-threatening) adverse reactions in dogs treated with STELFONTA included: lameness in the treated limb (6 dogs), injection site pain (4 dogs), wound formation (3 dogs), lethargy/depression (3 dogs), anorexia (2 dogs), infection at injection site (1 dog), pruritis (1 dog), and tachycardia (1 dog).

Adverse reactions associated with use of the required concomitant corticosteroids were similarly reported in STELFONTA and untreated control
dogs and included elevated alkaline phosphatase, polyuria, and polydipsia.

Wound Formation

Tumor observations were conducted at 2, 4, 8, and 24 hours and 4 days after treatment. The 81 dogs treated with STELFONTA on Day 0 were reported most frequently with swelling, bruising, pain and heat at all tumor observation timepoints. The following were reported at 24 hours post treatment:

- Swelling: 97.5% (79/81 dogs)
- Bruising: 91.4% (74/81 dogs)
- Pain: 69.1% (56/81 dogs)
- Heat: 53.1% (43/81 dogs)

At 24 hours post treatment, intact skin was reported in 71.6% (58/81 dogs) of STELFONTA® (tigilanol tiglate injection) treated dogs. On Day 4 intact skin was reported in 17.3% (14/81 dogs) of STELFONTA treated dogs. On Day 4, the following observations were reported with the highest frequency:

- Necrosis: 55.6% (45/81 dogs)
- Crater pockets: 37.0% (30/81 dogs)
- Exudate: 37.0% (30/81 dogs)
- Eschar: 28.4% (23/81 dogs)
- Ulceration: 11.1% (9/81 dogs)

A wound healing assessment was performed on the effectiveness dataset which included 80 dogs in the STELFONTA group and 38 dogs in the untreated control group. Wounds developed in 92.5% (74/80) of STELFONTA treated dogs and 2.6% (1/38) of untreated control dogs by Day 7. On Day 28, the presence of wounds was 40% (32/80) in the STELFONTA group and 2.6% (1/38) in the untreated control group. On Day 42 and Day 84, the presence of wounds was 27.1% (16/59) and 1.8% (1/57), respectively, in the STELFONTA group.

Exudate from the treated site including serous, serosanguinous, sanguineous, seropurulent, and purulent discharges were seen mainly on Day 7 and to a lesser extent on Day 14. Sloughing of the treated site was observed from Day 7 to Day 42, with decreasing frequency after Day 7. Peripheral pitting or non-pitting edema and erythema of the surrounding area were observed from Day 7 to Day 28, with decreasing intensity and frequency after Day 7. Necrotic eschar and epithelialization of the treated site was observed from Day 7 to Day 84, with decreasing frequency after Day 14. Granulation or hyper-granulation of the treated site was observed from Day 7 to Day 84, with decreasing frequency after Day 14.

The average wound size at Day 7 for a STELFONTA treated dog was 3.3 cm x 2.4 cm (original average tumor size 1.9 x 1.6 x 0.9 cm). On Day 28, the average wound size was 2.0 x 1.4 cm.

The largest total wound for a STELFONTA treated dog was reported seven days after treatment. The treated tumor was located on the left caudal stifle and the original tumor size measured 2.4 x 2.1 x 1.4 cm. The wound area initially consisted of three individual wounds recorded on the treated limb (both medial and lateral sides): 7.5 x 4.5 cm, 7.0 x 3.5 cm, and 11.5 x 7.0 cm. The wounds had reduced to 3.5 x 1.4 cm, 3.9 x 1.5 cm, and 9.7 x 4.3 cm 28 days after treatment, and 0.5 x 0.7 cm and 2.5 x 2.9 cm 42 days after treatment and were no longer present at 84 days after treatment.

One dog treated with STELFONTA was reported with an extensive wound formation (wound size 25.0 x 9.5 cm) with severe tissue slough (Grade 3) nine days after treatment of a mast cell tumor on the left metacarpal area (original tumor size 2.5 x 1.9 x 1.3 cm). The wound extended proximally up the leg to the shoulder and required bandaging of the leg and antibiotics. Scar contracture formed, requiring treatment under sedation to release the scar tissue. Clinical pathology abnormalities included elevated band neutrophils, anemia, and hypoalbuminemia. The wound had not fully healed by the end of the study 89 days after treatment. See pictures below comparing progression of this extensive
wound formation versus commonly observed wound progression.

One dog treated with STELFONTA was reported with a bacterial infection and cellulitis in the right rear leg 9 days after treatment of a mast cell tumor on the right rear paw. There was bruising of the upper thigh and necrotic skin on the caudal right thigh and cranial aspect of the hock. Bloody discharge under the necrotic tissue revealed rod bacteria and toxic neutrophils. The dog was treated with intravenous fluids and antibiotics.

Systemic Mast Cell Degranulation and Death

Two dogs from two separate pilot studies died from a suspected mast cell degranulation reaction. Both dogs were treated with STELFONTA for a subcutaneous mast cell tumor located above the hock and did not receive the concomitant medications as prescribed.

In a pilot field study, one dog with a large (10 cm³) subcutaneous mast cell tumor on the right hip was treated with STELFONTA. The dog had a partial Response Evaluation Criteria in Solid Tumors Guideline (RECIST)2 response to the initial STELFONTA injection and was re-treated with STELFONTA, 30 days following the initial injection. The patient did not receive any of the recommended concomitant medications of prednisolone, chlorpheniramine and famotidine from 24 hours after the second STELFONTA injection. On Day 2 following the second STELFONTA injection, the dog became anorexic, painful, and lethargic and had marked swelling of the right hind limb extending to the chest with hemorrhagic, ruptured blisters near the hock joint. Blood work showed anemia, hypoproteinemia, liver enzyme elevations, and white blood cell changes (leukocytosis, neutrophilia, monocytosis, and thrombocytopenia). The dog was hospitalized, received a blood transfusion, and was administered intravenous fluids, prednisolone, chlorpheniramine and tramadol. Pitting edema progressed to the neck by four days following treatment. Despite supportive care, the dog died five days following treatment likely due to degranulation of the mast cell tumor and internal necrotic discharge of the tumor.

In a separate pilot field study, one dog with a moderate (2.53 cm3) subcutaneous mast cell tumor on the left caudal hindlimb was treated with STELFONTA. The dog was treated with chlorpheniramine and meloxicam on treatment day (Day 0) and Day 1 only. The dog did not receive further concomitant medication. On Day 3 the dog was lethargic and there was significant edema at the injection site. While intravenous fluid and antibiotic therapy was initiated on Day 3, the dog rapidly deteriorated and died on the following day likely due to degranulation of the mast cell tumor. Pathology findings included widespread cellulitis, panniculitis (likely of bacterial origin), and septic peritonitis.

To report suspected adverse reactions, to obtain a Safety Data Sheet (SDS), or for technical assistance, call 800-338-3659. For additional information about adverse drug experience reporting for animal drugs, contact the FDA at 1-888-FDA-VETS or www.fda.gov/reportanimalae.

INFORMATION FOR DOG OWNERS

Owners should be given the Client Information Sheet to read before STELFONTA is administered and should be advised to observe their dog for potential side effects, including signs of degranulation and excessive wound formation, as described in the sheet. Advise dog owners about possible adverse reactions, when to contact a veterinarian, and how to care for the treated tumor site. Some discharge from the site following treatment is expected. The site can be cleaned with warm water as necessary. Advise owners to wear disposable gloves when cleaning the area.

CLINICAL PHARMACOLOGY

Mechanism of Action

In non-clinical pharmacology studies, tigilanol tiglate has been shown to have three inter-related effects that are responsible for its anti-tumor effectiveness. The first effect is to cause oncolysis of tumor cells that are in direct contact with tigilanol tiglate. The oncolysis occurs within the first hours following treatment and results from the disruption of mitochondrial functioning. Secondly, at the same time, tigilanol tiglate activates a protein kinase C (PKC) signaling cascade which propagates throughout the tumor, resulting in an acute inflammatory response with swelling and erythema extending to the tumor margins and immediate surroundings. This inflammatory response is normal and necessarily contributes to the activity of tigilanol tiglate by (a) restricting blood and oxygen supply to the tumor (causing localized hypoxia) and (b) recruiting and activating innate immune cells (principally neutrophils and macrophages), which then target the tumor and release reactive oxygen species, proteases, and cytokines that function in an antimicrobial role. This acute inflammatory response generally resolves within 48 to 96 hours. The third component of the antitumor activity of tigilanol tiglate is associated with direct effects of the drug in increased permeability of the tumor vasculature (via activation of the Beta-II isoform of PKC) leading to tumor vascular destruction. The resulting outcome is tumor destruction with a deficit or wound remaining where the tumor was located. Complete healing of the resulting wound following tumor destruction by STELFONTA is typically within 6 weeks.

Pharmacokinetics

Pharmacokinetic properties of STELFONTA were evaluated in a pilot study monitoring systemic levels following intratumoral injection, with a dose delivered according to the size of the mast cell tumor. A dose of 0.5 mg/cm3 (0.5 mL/cm3) was used in dogs with tumor volumes ranging from 0.1 to 6.8 cm3 resulting in doses ranging from 0.002 mg/kg to 0.145 mg/kg and total doses ranging from 0.05 mg to 3.4 mg per dog. A total of 6 cutaneous and 5 subcutaneous mast cell tumors were treated in 10 dogs (one dog had two tumors treated consecutively). The following range of pharmacokinetic parameters were determined for STELFONTA in plasma: 1) elimination half-life (t½): 2.85 to 36.87 hours; 2) maximum plasma concentration (Cmax): 0.356 ng/mL to 13.8 ng/mL; and 3) area under the plasma concentration time-curve to the last quantifiable plasma concentration (AUClast): 2.25 h*ng/mL to 31.24 h*ng/mL. There was no relationship between drug exposure (Cmax and AUClast) with tumor location (cutaneous or subcutaneous) or with total dose. In an evaluation of the pharmacokinetic data from the 5 dogs with cutaneous tumors, dose levels ranged from 0.002 mg/kg to 0.145 mg/kg. The highest Cmax was 11.1 ng/mL and the highest AUClast was 31.24 h*ng/mL at a dose of 0.125 mg/kg. For the other 5 dogs with subcutaneous tumors, doses ranged from 0.049 mg/kg to 0.094 mg/kg. The highest Cmax was 13.8 ng/mL and the highest AUClast was 30.81 h*ng/mL at a dose of 0.094 mg/kg.

EFFECTIVENESS

The effectiveness of STELFONTA was evaluated in a well-controlled, multi-center, randomized, double-masked, field study in client-owned dogs. Enrolled dogs had non-metastatic World Health Organization stages Ia (one tumor confined to the dermis, without regional lymph node involvement) and IIIa (multiple dermal tumors; large infiltrating tumors without regional lymph node involvement) mast cell tumors that were (i) cutaneous, or (ii) subcutaneous and located at or distal to the elbow or the hock). A total of 123 client-owned dogs with a mast cell tumor
measuring less than or equal to 10 cm3 were randomized to treatment with a single injection of STELFONTA (n=81) or untreated control (n=42). On the day of treatment, the average tumor volume was 1.7 cm3 (range 0.1 to 9.8 cm3).

A total of 118 dogs were included in the effectiveness analysis; 80 dogs were in the STELFONTA group and 38 dogs were in the untreated control group. Response to treatment was evaluated using the RECIST2, where complete response (CR) is resolution of the target tumor, partial response (PR) is at least a 30% decrease in the longest diameter of target tumor, stable disease (SD) is a decrease of less than 30% or increase of less than 20% of the longest diameter of the target tumor, and progressive disease (PD) is greater than a 20% increase in the longest diameter of the target tumor.

The primary effectiveness variable compared CR rates of the target tumor between groups 28 days after treatment. At 28 days after treatment, a statistically significantly greater proportion of dogs in the STELFONTA treated group (60/80; 75%) achieved CR compared to dogs in the untreated control group (2/38; 5.3%) (p<0.0001). An objective tumor response (CR + PR) was observed in 64/80 (80%) of the STELFONTA treated dogs. Of the 60 dogs in the STELFONTA group that experienced CR at Day 28, response assessment was conducted for 59 dogs at Day 42 and for 57 dogs at Day 84. At Day 42, 59/59 (100%) were disease-free at the injection site, and at Day 84, 55/57 (96%) were disease-free at the injection site.

For all dogs, corticosteroids (prednisone or prednisolone) were initiated 2 days prior to treatment at a dose of 0.5 mg/kg orally twice daily and continued for 7 days total (2 days before, on the day of treatment and 4 days after treatment), then 0.5 mg/kg once daily for an additional 3 days. An H1 receptor blocking agent (diphenhydramine [2 mg/kg orally twice daily]) and H2 receptor blocking agent (famotidine [0.5 mg/kg orally twice daily]) were initiated on the day of treatment and continued for 7 days.

Other medications prescribed based on veterinary discretion included antibiotics, analgesics, and sedatives. The majority of antibiotics were used to treat injection site infections. The majority of analgesics were used to treat tumor pain and were mainly initiated on the day of or day after treatment. Sedatives were used for treatment administration, conducting diagnostics, anxiety, and temperament issues.

Quality of Life (QoL)3 was assessed by owners throughout the study and the mean scores for the QoL assessment was similar between the STELFONTA and untreated control groups at all time points.

Eighteen of the 20 STELFONTA treated dogs without CR received a second treatment. Twenty-eight days following the second treatment, CR was observed in 8/18 (44.4%) of these dogs. Forty-two days following the second treatment, CR was observed in 7/18 (38.9%) of treated dogs.

TARGET ANIMAL SAFETY

The margin of safety and toxicity of STELFONTA was evaluated in one laboratory safety study and one laboratory cardiovascular study utilizing final market formulation, and one pilot field study that used non-commercial formulation.

Laboratory Safety Study

In a 4-week laboratory safety study, 48 healthy Beagle dogs 6 to 8 months old were administered STELFONTA intravenously over a 15-minute infusion once a week for four weeks on Days 1, 8, 15, and 22, at doses of 0, 0.025, 0.05, or 0.075 mg/kg body weight (ranges between 0.02-0.036, 0.039-0.056, and 0.06-0.08 mg/kg, respectively due to dosing variability). Control dogs (0 mg/kg) received a vehicle control at a volume equal to the 0.075 mg/kg dose. The intravenous route was chosen for this study because subcutaneous injection was too toxic and intratumoral administration was not possible.

There were twelve dogs per group (6 male, 6 female). Four dogs/sex/group were necropsied two days following the last dose and two dogs/sex/group were necropsied following a 2-week recovery period.

All dogs survived the study, and there were no STELFONTA-related effects on body weight, body temperature, ophthalmic exam, electrocardiographic parameters, and organ weights.

The following were observed only in dogs in the groups administered STELFONTA: decreased food consumption from Days 22-29, vomiting/retching during infusion or immediately post-infusion, wound formation at the infusion site after the second or third dose, decrease in activity sporadically throughout the study, and elevations in alanine aminotransferase on Day 23. The following were observed in all groups, including vehicle control and increased in a dose dependent manner: limited use of the leg that received the infusion occurred soon after dosing, weakness after the first dose, salivation and infusion site edema and erythema increased in frequency and severity throughout the study, and tremors occurred immediately post-infusion and increased in severity with dose.

Vomiting, retching, or tremors were typically transient and resolved within 1 hour of dosing while salivation also typically resolved within 4 hours. Loose feces were observed in all groups in a non-dose dependent manner. Polydipsia occurred in the control, 0.05 and 0.075 mg/kg groups. Trending towards decreasing hematocrit (but still within reference intervals) was observed in all groups. One dog in the 0.05 mg/kg group was mildly anemic during recovery. Monocytosis and elevated fibrinogen were seen on Days 2 and 23 in a dosedependent manner.

Gross pathology findings at the infusion site included inflammation, redness, and thickening of the skin. Correlative histopathology findings of the infusion site included hemorrhage, edema, inflammation, mixed cell infiltration, fibrosis, and chronic organizing thrombosis. Only one of the recovery dogs had changes at the infusion site consisting of proliferation of the intima. One dog in the 0.075 mg/kg group had a severe wound, confirmed on histopathology as ulcerative inflammation and severe necrosis with bacteria present. Gross pathology findings also included red, mottled, firm, and enlarged lymph nodes in all dose groups, including recovery dogs, confirmed on histopathology as inflammation, lymphoid hypercellularity, hemorrhage, and sinus histiocytosis. Pituitary cysts were observed in 7 dogs in all STELFONTA treated groups. One dog each from the 0.075 mg/kg group was observed to have kidney tubular vacuolation, dilation of the ventricles of the brain, and chronic inflammation of both the left thigh skeletal muscle and left sciatic nerve.

Laboratory Cardiovascular Study

In a 12-day laboratory cardiovascular study, 4 healthy male conscious telemeterized Beagle dogs approximately 2-4 years old were administered STELFONTA as a single intravenous infusion. Treatment consisted of four groups: vehicle control and STELFONTA at doses of 0.01, 0.025 and 0.075 mg/kg body weight. All four dogs received all treatments with at least a 3-day wash-out period.

All dogs survived the study and there were no STELFONTA-related effects on body temperatures, blood pressure, or electrocardiograms. The following were observed only after administration of STELFONTA in all dose groups: salivation, vocalization, incoordination, tremors, red feces, and decreased feces output. Retching, vomiting, incoordination, and changes in activity levels (increased and decreased) occurred in the 0.075 mg/kg group only. Tachycardia was seen for the first 2.5 hours after the 0.075 mg/kg dose only. The following were observed after administration of control or STELFONTA: excessive panting, decreased appetite, and limited usage/swelling of leg or paw. All dogs lost weight during the study. Clinical signs resolved around 4 hours post dosing.

Pilot Field Study

In a 28-day unmasked field study, 10 client-owned dogs, 6-14 years old were administered tigilanol tiglate (non-commercial formulation) once as an intratumoral injection at a dose of 0.5 mg tigilanol tiglate per cubic centimeter (cm3) of tumor volume, not exceeding 0.25 mg/kg body weight (maximum dose of 5 mg). One dog was enrolled a second time to treat a second mast cell tumor after successful treatment of the first tumor. See pharmacokinetic results from this study under Clinical Pharmacology.

The most common observations after tigilanol tiglate administration were injection site reactions including necrosis, swelling (localized edema and edema extending well beyond the tumor injection site), pain, restlessness, inflammation, erythema, bleeding ulcerations, bruising/discoloration, sloughing of tissue, open wound, mild drainage, malodor, and presence of granulation tissue. Three dogs experienced dermatitis with or without skin necrosis in a region nearby but distinct from the tumor injection site. One dog experienced non-weight bearing lameness, muscle atrophy and enlarged popliteal lymph node. One dog vomited after administration. Three dogs required longer healing times beyond 28 days, with the longest requiring 5 months. Hypoalbuminemia was observed in 5 dogs with hypoproteinemia observed in 1 of these 5 dogs on Day 7 and was resolved by Day 28.

STORAGE INFORMATION

Store STELFONTA vials refrigerated at 2°C to 8°C (35°F to 46°F).

Do not freeze.

Keep the vial in the carton at all times to protect the vial from light.

For single use only.

Dispose of any unused product in accordance with disposal for routine medical waste.

HOW SUPPLIED

STELFONTA is supplied as a sterile, colorless liquid in a 5 mL clear, single-use glass vial containing 2 mL of STELFONTA at a concentration of 1 mg/mL tigilanol tiglate in sterile water for injection.

REFERENCES

1. Veterinary Cooperative Oncology Group – common terminology criteria for adverse events (VCOG-CTCAE) following chemotherapy or biologic antineoplastic therapy in dogs and cats v1.1. Vet Compar Oncol. 20 Jul 2011.

2. Eisenhauer EA, Therase P, Bogaerts J, Schwartz LH, Sargent D, Ford R, Dancey J, Arbuck S, Gwyther S, Mooney M, Rubinstein L, Shankar L, Dodd L, Kaplan R, Lacombe D, Verweij J. New response evaluation criteria in solid tumors: revised RECIST guideline (version 1.1), Eur J Cancer. 2009; 45(2):228-247.

3. Lynch S, Savary-Bataille K, Leeuw B, Argyle DJ. Development of a questionnaire assessing health-related quality-of-life in dogs and cats with cancer. Vet Compar Oncol. 2011; 9 (3):172-82.

Approved by FDA under NADA # 141-541

STELFONTA® is a registered trademark of QBiotics Group Limited.

Distributed by Virbac AH, Inc.

P.O Box 162059,

Fort Worth, Texas 76161.

Tel. 1-800-338-3659

Version date: August 2020